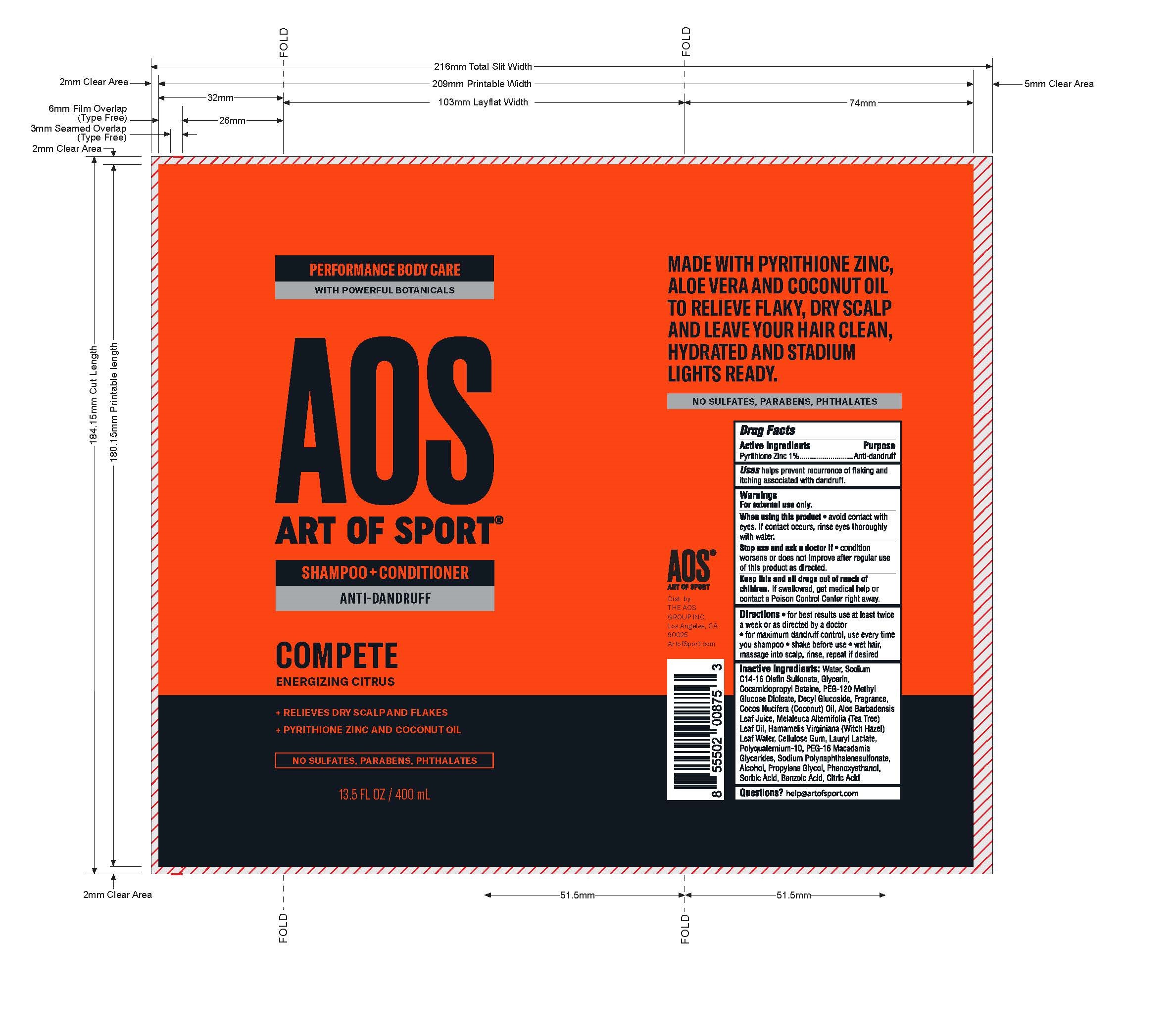 DRUG LABEL: Art of Sport Anti Dandruff Compete
NDC: 72698-811 | Form: SHAMPOO
Manufacturer: AOS GROUP INC, THE
Category: otc | Type: HUMAN OTC DRUG LABEL
Date: 20230130

ACTIVE INGREDIENTS: PYRITHIONE ZINC 100 g/1 mL
INACTIVE INGREDIENTS: CARBOXYMETHYLCELLULOSE SODIUM; LAURYL LACTATE; PROPYLENE GLYCOL; BENZOIC ACID; ALCOHOL; COCONUT OIL; ALOE VERA LEAF; HAMAMELIS VIRGINIANA LEAF WATER; PEG-16 MACADAMIA GLYCERIDES; PHENOXYETHANOL; SORBIC ACID; CITRIC ACID MONOHYDRATE; GLYCERIN; COCAMIDOPROPYL BETAINE; WATER; SODIUM C14-16 OLEFIN SULFONATE; PEG-120 METHYL GLUCOSE DIOLEATE; DECYL GLUCOSIDE; TEA TREE OIL

ART OF SPORT SHAMPOO and CONDITIONER ANTI-DANDRUFF.

Active Ingredients
Pyrithione Zinc 1%

Purpose
Anti-dandruff

INDICATIONS AND USAGE

Uses help prevent recurrence of flaking and itching associated with dandruff.

Warnings
For external use only.

When using this product * avoid contact with eyes. If contact occurs, rinse eyes thoroughly with water.

Stop use and ask a doctor if * condition worsens or does not improve after regular use of this product as directed.

KEEP OUT OF REACH OF CHILDREN

Keep this and all drugs out of reach of children. If swallowed, get medical help or contact a Posion Control Center right away.

DOSAGE AND ADMINISTRATION

Directions * for best results use at least twice a week or as directed by a doctor * for maximum dandruff control, use every time you shampoo * shake before use * wet hair, massage into scalp, rinse, repeat if desired.

INACTIVE INGREDIENT

Inactive ingredients: Water, Sodium C14-16 Olefin Sulfonate, Glycerin, Cocamidopropyl Betaine, PEG-120 Methyl Glucose Dioleate, Decyl Glucoside, Fragrance, Cocos Nucifera (Coconut) Oil, Aloe Barbadensis Leaf Juice, Melaleuca Alternifolia (Tea Tree) Leaf Oil, Hamamelis Virginiana (Witch Hazel) Leaf Water, Cellulose Gum, Lauryl Lactate, Polyquaternium-10, PEG-16 Macadamia Glycerides, Sodium Polynaphthalenesulfonate, Alcohol, Propylene Glycol, Phenoxyethanol, Sorbic Acid, Benzoic Acid, Citric Acid

Questions? help@artofsport.com